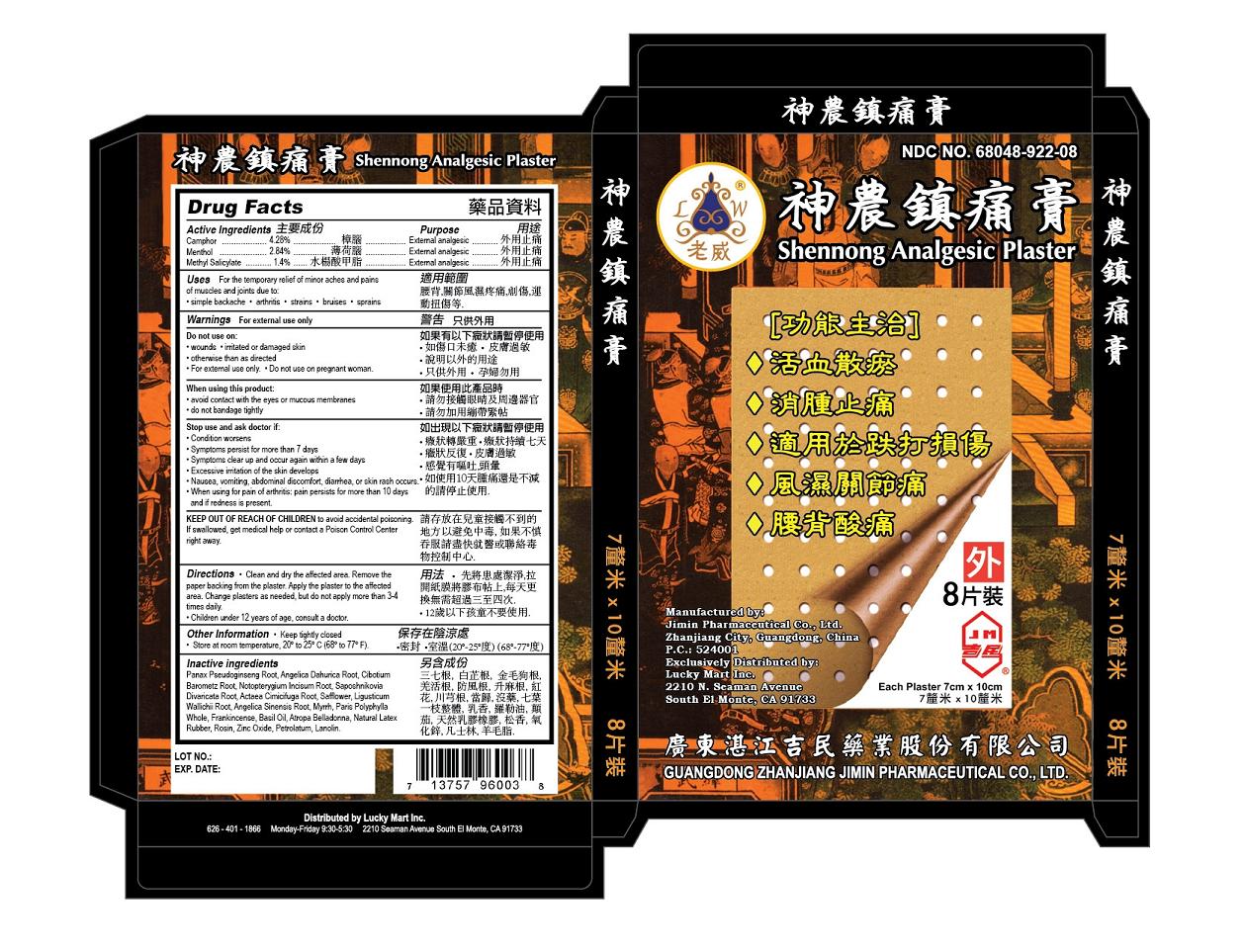 DRUG LABEL: Shennong Analgesic Plaster
NDC: 68048-922 | Form: PLASTER
Manufacturer: Guangdong Zhanjiang Jimin Pharmaceutical Co. Ltd
Category: otc | Type: HUMAN OTC DRUG LABEL
Date: 20160316

ACTIVE INGREDIENTS: CAMPHOR (SYNTHETIC) 4.28 mg/100 mg; MENTHOL 2.84 mg/100 mg; METHYL SALICYLATE 1.4 mg/100 mg
INACTIVE INGREDIENTS: PANAX PSEUDOGINSENG ROOT; ANGELICA DAHURICA ROOT; CIBOTIUM BAROMETZ ROOT; NOTOPTERYGIUM INCISUM ROOT; SAPOSHNIKOVIA DIVARICATA ROOT; ACTAEA CIMICIFUGA ROOT; SAFFLOWER; LIGUSTICUM WALLICHII ROOT; ANGELICA SINENSIS ROOT; MYRRH; PARIS POLYPHYLLA WHOLE; FRANKINCENSE; BASIL OIL; ATROPA BELLADONNA; NATURAL LATEX RUBBER; ROSIN; ZINC OXIDE; PETROLATUM; LANOLIN

Guangdong Zhanjiang Jimin Pharmaceutical Co, Ltd

Active Ingredients

Camphor 4.28%

Menthol 2.84%

Methyl Salicylate 1.4%

Purpose

Camphor External Analgesic

Menthol External Analgesic

Methyl Salicylate External Analgesic

Uses

For the temporary relief of minor aches and pains of muscles and joints due to:

Simple backache, arthritis, strains, bruises, sprains.

Warnings

For external use only.

Do not use on pregnant woman.

Do not use

on wounds, irritated or damaged skin, otherwise than as directed.

When using this product

Avoid contact with the eyes or mucous membranes.

Do not bandage tightly.

Stop use and ask a doctor if

Condition worsens.

Symptoms persist for more than 7 days.

Symptoms clear up and occur again within a few days.

Excessive irritation of the skin develops.

Nausea, vomiting, abdominal discomfort, diarrhea or skin rash occurs.

When using for pain of arthritis: pain persists for more than 10 days and if redness is present.

Keep out of reach of children to avoid accidental poisoning. If swallowed, get medical help or contact a Poison Control Center right away.

Directions

Clean and dry the affected area. Remove the paper backing from the plaster. Apply the plaster to the affected area. Change plasters as needed, but do not apply more than 3 to 4 times daily.

Children under 12 years of age: contact a doctor.

Other Information

Keep tightly closed.

Store at room temperature, 20 to 25 °C (68-77 °F)

Inactive Ingredients

PANAX PSEUDOGINSENG ROOT, ANGELICA DAHURICA ROOT, CIBOTIUM BAROMETZ ROOT, NOTOPTERYGIUM INCISUM ROOT, SAPOSHNIKOVIA DIVARICATA ROOT, ACTAEA CIMICIFUGA ROOT, SAFFLOWER, LIGUSTICUM WALLICHII ROOT, ANGELICA SINENSIS ROOT, MYRRH, PARIS POLYPHYLLA WHOLE, FRANKINCENSE, BASIL OIL, ATROPA BELLADONNA, NATURAL LATEX RUBBER, ROSIN, ZINC OXIDE, PETROLATUM, LANOLIN